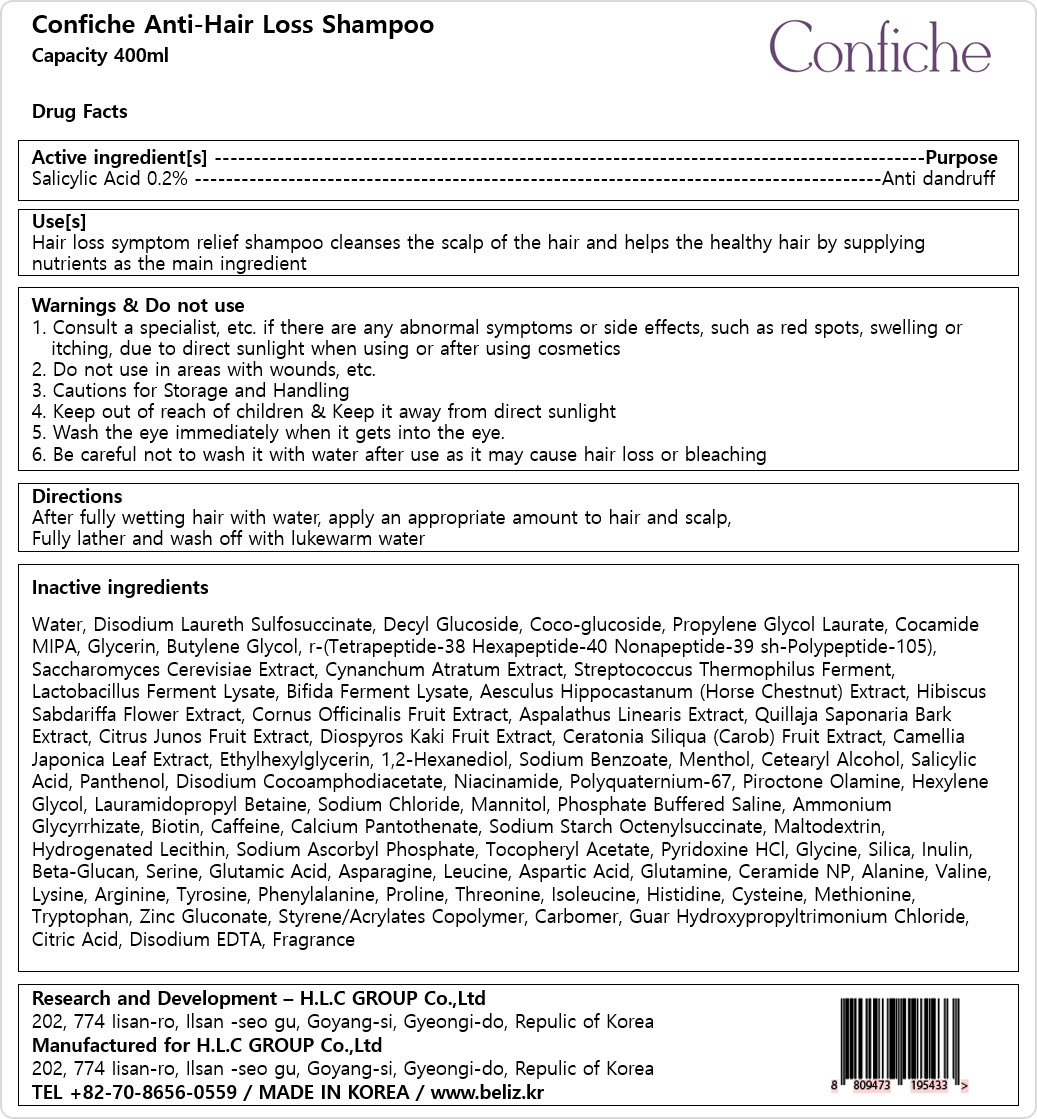 DRUG LABEL: Confiche Anti-Hair LossShampoo
NDC: 81555-301 | Form: SHAMPOO
Manufacturer: H.L.C GROUP Co., ltd
Category: otc | Type: HUMAN OTC DRUG LABEL
Date: 20231124

ACTIVE INGREDIENTS: SALICYLIC ACID 2 mg/100 mL
INACTIVE INGREDIENTS: LEUCINE; ASPARTIC ACID; GLUTAMINE; CERAMIDE NP; VALINE; ARGININE; THREONINE; ISOLEUCINE; GLYCERIN; VINCETOXICUM ATRATUM WHOLE; QUILLAJA SAPONARIA BARK; CAROB; 1,2-HEXANEDIOL; ALANINE; LYSINE; TYROSINE; PHENYLALANINE; PROLINE; HISTIDINE; CYSTEINE; METHIONINE; ZINC GLUCONATE; CITRIC ACID MONOHYDRATE; ESCHERICHIA COLI; DECYL GLUCOSIDE; COCO GLUCOSIDE; CITRUS JUNOS FRUIT; BUTYLENE GLYCOL; STREPTOCOCCUS THERMOPHILUS; PERSIMMON; PIROCTONE OLAMINE; MANNITOL; CALCIUM PANTOTHENATE; ALUMINUM STARCH OCTENYLSUCCINATE; SODIUM ASCORBYL PHOSPHATE; .ALPHA.-TOCOPHEROL ACETATE; EDETATE DISODIUM ANHYDROUS; LIMOSILACTOBACILLUS FERMENTUM; SODIUM CHLORIDE; GLYCINE; SILICON DIOXIDE; TRANSFORMING GROWTH FACTOR BETA RECEPTOR TYPE 3; SERINE; ASPARAGINE; MENTHOL; CETOSTEARYL ALCOHOL; LAURAMIDOPROPYL BETAINE; AMMONIUM GLYCYRRHIZATE; GLUTAMIC ACID; BIFIDOBACTERIUM BIFIDUM R0071; TETRAPEPTIDE-7; DISODIUM LAURETH SULFOSUCCINATE; COCO MONOISOPROPANOLAMIDE; SACCHAROMYCES CEREVISIAE; BIOTIN; CAFFEINE; HYDROGENATED SOYBEAN LECITHIN; INULIN; SODIUM PHOSPHATE, DIBASIC, ANHYDROUS; WATER; PROPYLENE GLYCOL MONOLAURATE; HORSE CHESTNUT; HIBISCUS SABDARIFFA FLOWER; CORNUS OFFICINALIS FRUIT; ASPALATHUS LINEARIS LEAF; CAMELLIA JAPONICA LEAF; ETHYLHEXYLGLYCERIN; SODIUM BENZOATE; PANTHENOL; DISODIUM COCOAMPHODIACETATE; NIACINAMIDE; MALTODEXTRIN; HEXYLENE GLYCOL; PYRIDOXINE HYDROCHLORIDE; TRYPTOPHAN; STYRENE/ACRYLAMIDE COPOLYMER (MW 500000); CARBOXYPOLYMETHYLENE; GUAR HYDROXYPROPYLTRIMONIUM CHLORIDE (1.7 SUBSTITUENTS PER SACCHARIDE); FRAGRANCE 13576

81555-301 CONFICHE ANTI-HAIR LOSS SHAMPOO

Active ingredients

Salicylic Acid 0.2%

Purpose

Salicylic Acid 0.2% -Anti dandruff

Uses

Hair loss symptom relief shampoo cleanses the scalp of the hair and helps the healthy hair by supplying nutrients as the main ingredient

Warnings

1. Consult a specialist, etc. if there are any abnormal symptoms or side effects, such as red spots, swelling or

itching, due to direct sunlight when using or after using cosmetics

2. Do not use in areas with wounds, etc.

3. Cautions for Storage and Handling

4. Keep out of reach of children & Keep it away from direct sunlight

5. Wash the eye immediately when it gets into the eye.

6. Be careful not to wash it with water after use as it may cause hair loss or bleaching

Warnings

Consult a specialist, etc. if there are any abnormal symptoms or side effects, such as red spots, swelling or

itching, due to direct sunlight when using or after using cosmetics

Warnings

Wash the eye immediately when it gets into the eye.

Warnings

Keep out of reach of children & Keep it away from direct sunlight

Warnings

Do not use in areas with wounds, etc

Directions

After fully wetting hair with water, apply an appropriate amount to hair and scalp,

Fully lather and wash off with lukewarm water

Inactive ingredients

Water, Disodium Laureth Sulfosuccinate, Decyl Glucoside, Coco-glucoside, Propylene Glycol Laurate, Cocamide

MIPA, Glycerin, Butylene Glycol, r-(Tetrapeptide-38 Hexapeptide-40 Nonapeptide-39 sh-Polypeptide-105),

Saccharomyces Cerevisiae Extract, Cynanchum Atratum Extract, Streptococcus Thermophilus Ferment,

Lactobacillus Ferment Lysate, Bifida Ferment Lysate, Aesculus Hippocastanum (Horse Chestnut) Extract, Hibiscus

Sabdariffa Flower Extract, Cornus Officinalis Fruit Extract, Aspalathus Linearis Extract, Quillaja Saponaria Bark

Extract, Citrus Junos Fruit Extract, Diospyros Kaki Fruit Extract, Ceratonia Siliqua (Carob) Fruit Extract, Camellia

Japonica Leaf Extract, Ethylhexylglycerin, 1,2-Hexanediol, Sodium Benzoate, Menthol, Cetearyl Alcohol, Salicylic

Acid, Panthenol, Disodium Cocoamphodiacetate, Niacinamide, Polyquaternium-67, Piroctone Olamine, Hexylene

Glycol, Lauramidopropyl Betaine, Sodium Chloride, Mannitol, Phosphate Buffered Saline, Ammonium

Glycyrrhizate, Biotin, Caffeine, Calcium Pantothenate, Sodium Starch Octenylsuccinate, Maltodextrin,

Hydrogenated Lecithin, Sodium Ascorbyl Phosphate, Tocopheryl Acetate, Pyridoxine HCl, Glycine, Silica, Inulin,

Beta-Glucan, Serine, Glutamic Acid, Asparagine, Leucine, Aspartic Acid, Glutamine, Ceramide NP, Alanine, Valine,

Lysine, Arginine, Tyrosine, Phenylalanine, Proline, Threonine, Isoleucine, Histidine, Cysteine, Methionine,

Tryptophan, Zinc Gluconate, Styrene/Acrylates Copolymer, Carbomer, Guar Hydroxypropyltrimonium Chloride,

Citric Acid, Disodium EDTA, Fragrance

Display Panel

81555-301